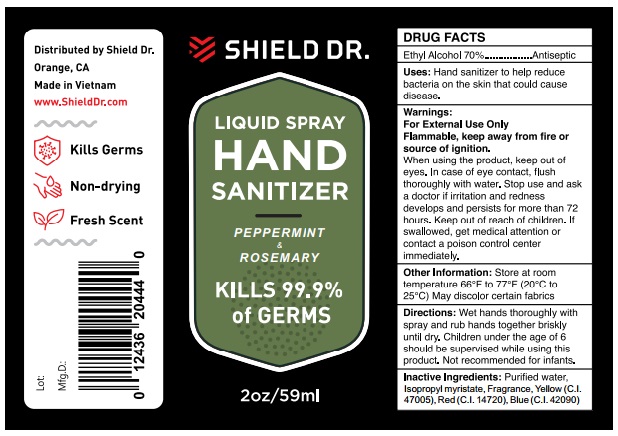 DRUG LABEL: Shield Dr.
NDC: 79633-305 | Form: LIQUID
Manufacturer: MEDIPHARCO PHARMACEUTICAL JOINT STOCK COMPANY
Category: otc | Type: HUMAN OTC DRUG LABEL
Date: 20200820

ACTIVE INGREDIENTS: ALCOHOL 70 mL/100 mL
INACTIVE INGREDIENTS: D&C YELLOW NO. 10; ISOPROPYL MYRISTATE; ROSEMARY OIL; FD&C BLUE NO. 1; POLYOXYL 40 HYDROGENATED CASTOR OIL; CARMOISINE; WATER; PEPPERMINT OIL

ACTIVE INGREDIENT

Ethyl Alcohol 70%

PURPOSE

Antiseptic

KEEP OUT OF REACH OF CHILDREN

If swallowed, get medical attention or contact poison control center immediately

INACTIVE INGREDIENT

Purified water, Isopropyl myristate, Fragrance, Yellow (C.I. 47005), Red (C.I. 14720), Blue (C.I. 42090)

DOSAGE AND ADMINISTRATION

Wet hand thoroughly with spray and rub hand together briskly until dry. Children under the age of 6 should be supervised while using this product. Not recommended for infants.

INDICATIONS AND USAGE

Hand sanitizer to help reduce bacteria on the skin it could cause disease

WARNINGS

For external use only.

Flammable, keep away from fire or source of ignition.

STORAGE AND HANDLING

Store at room temperature 66oF to 77oF (20oC to 25oC)

PACKAGE LABEL

59ml NDC:79633-305-59